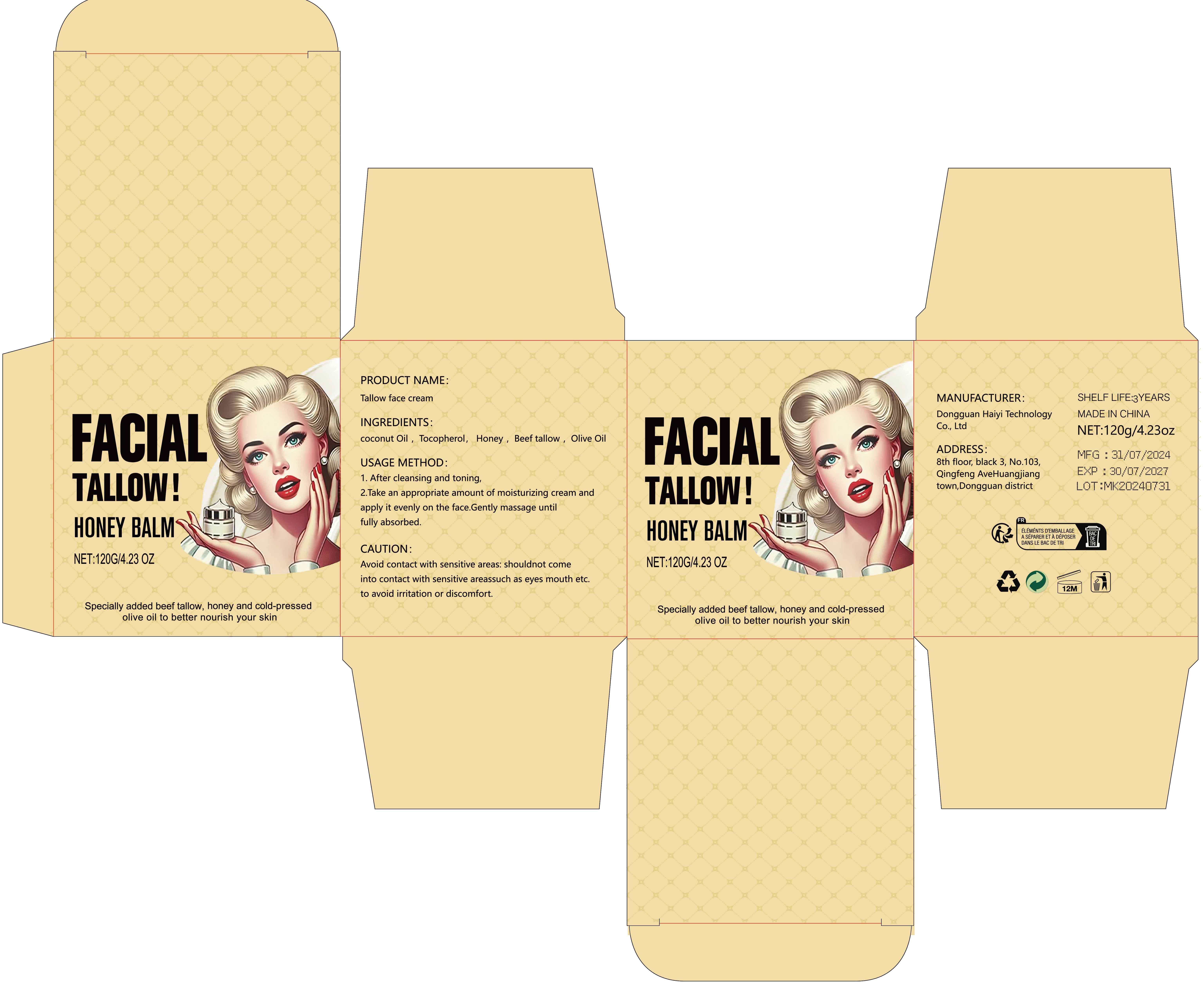 DRUG LABEL: Tallow face cream
NDC: 84732-057 | Form: CREAM
Manufacturer: Dongguan Haiyi Technology Co.,Ltd.
Category: otc | Type: HUMAN OTC DRUG LABEL
Date: 20241021

ACTIVE INGREDIENTS: .ALPHA.-TOCOPHEROL LINOLEATE, D- 1 mg/120 g
INACTIVE INGREDIENTS: BEEF TALLOW; COCONUT OIL; HONEY; OLIVE OIL

Active ingredient

Tocopherol

Inactive ingredient

coconut Oil , Honey , Beef tallow , Olive Oil

Purpose section

Nourishes, moisturizes and revitalizes the skin

Warning

Avoid contact with sensitive areas: shouldnot comeinto contact with sensitive areassuch as eyes mouth etc.

to avoid irritation or discomfort.

stop use

This product may cause allergic reactions in asmall number of people.
lf youexperience any discomfort,please stop using it immediately.

not use

Not suitable for use by children, pregnantor breast feeding people.

OUT OF CHILDREN

KEEP THE PRODUCT OUT OF REACH OF CHILDREN to

HOW TO USE

1. After cleansing and toning,

2.Take an appropriate amount of moisturizing cream andapply it evenly on the face.Gently massage untilfully absorbed.

Dosage

take an appropriateamount,Use 2-3 times a week